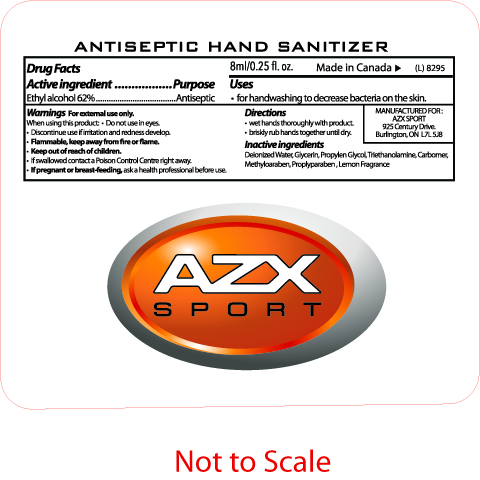 DRUG LABEL: Hand Sanitizer
NDC: 75887-001 | Form: GEL
Manufacturer: Aztex Enterprises
Category: otc | Type: HUMAN OTC DRUG LABEL
Date: 20181221

ACTIVE INGREDIENTS: ALCOHOL 5 mL/8 mL
INACTIVE INGREDIENTS: WATER; GLYCERIN; PROPYLENE GLYCOL; TROLAMINE; CARBOMER 1342; METHYLPARABEN; PROPYLPARABEN

Hand Sanitizer

Uses
for handwashing to decrease bacteria on the skin.

Warnings for external use only.
When using this product; Do not use in eyes.
Discontinue use if irritation and redness develop

Directions
wet hand thoroughly with product
briskly rub hands together until dry

Inactive Ingredients
Deionized water
Glycerin
Propylen Glycol
Triethanolamine
Carbomer
Methyloaraben
Proplyparaben
Lemon Fragrance

ACTIVE INGREDIENT

Drug Fact 8ml/0.25 fl.oz. Made in Canada -> (L) 8295
Active ingredient Purpose
Ethyl alcohol 62% Antisepctic

DOSAGE AND ADMINISTRATION

8ml/0.25 fl. oz.

Flammable, keep away from fire or flames.
Keep out of reach of children
If swallowed contact a Poison Control Center right away
If pregnant or breast feeding, ask a health care professional before use

PACKAGE LABEL

Anticeptic Hand Sanitizer
AZX SPORT
Manufactured for
AZX SPORT
925 Century Drive
Burlington, ON L7L 5LB